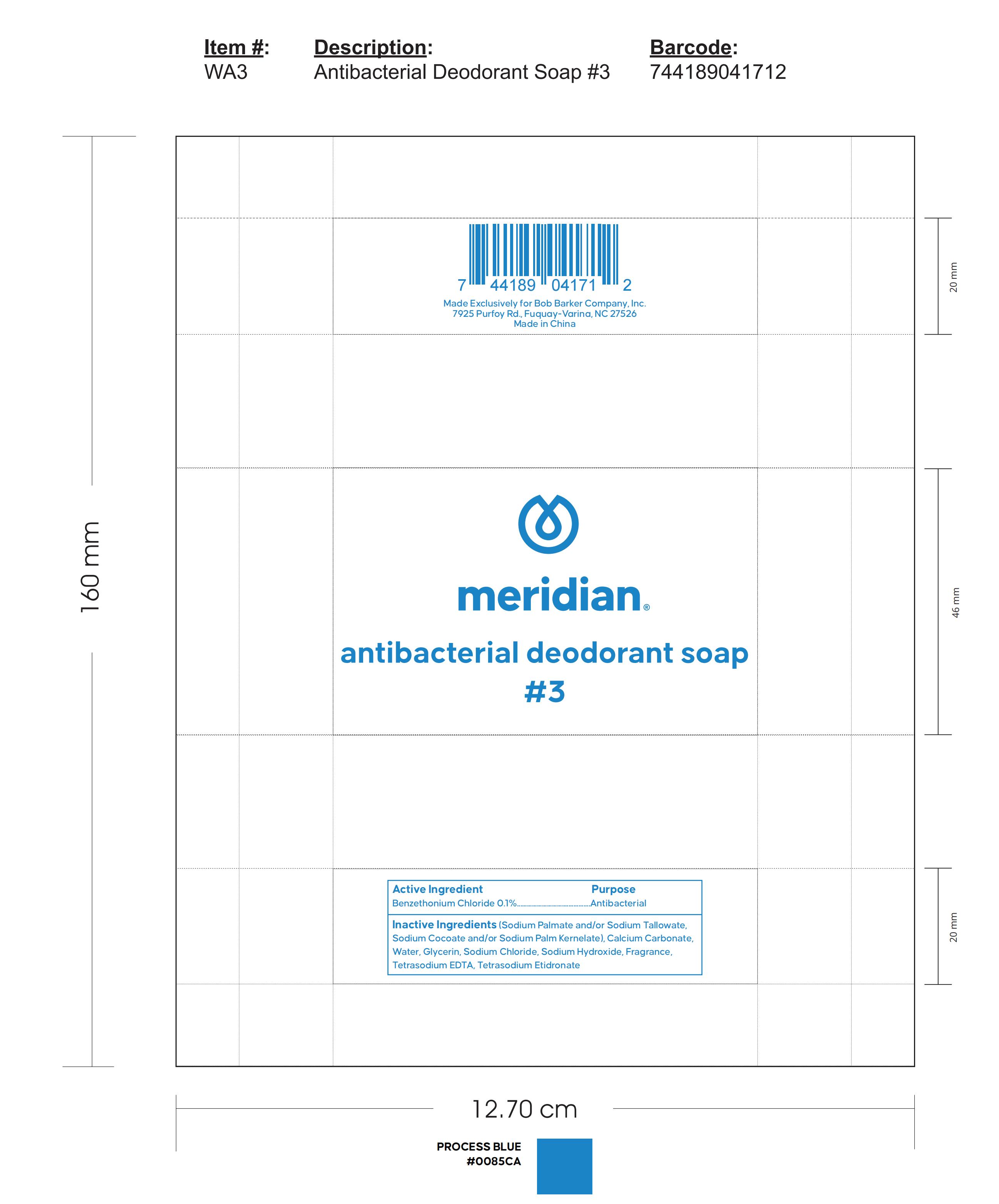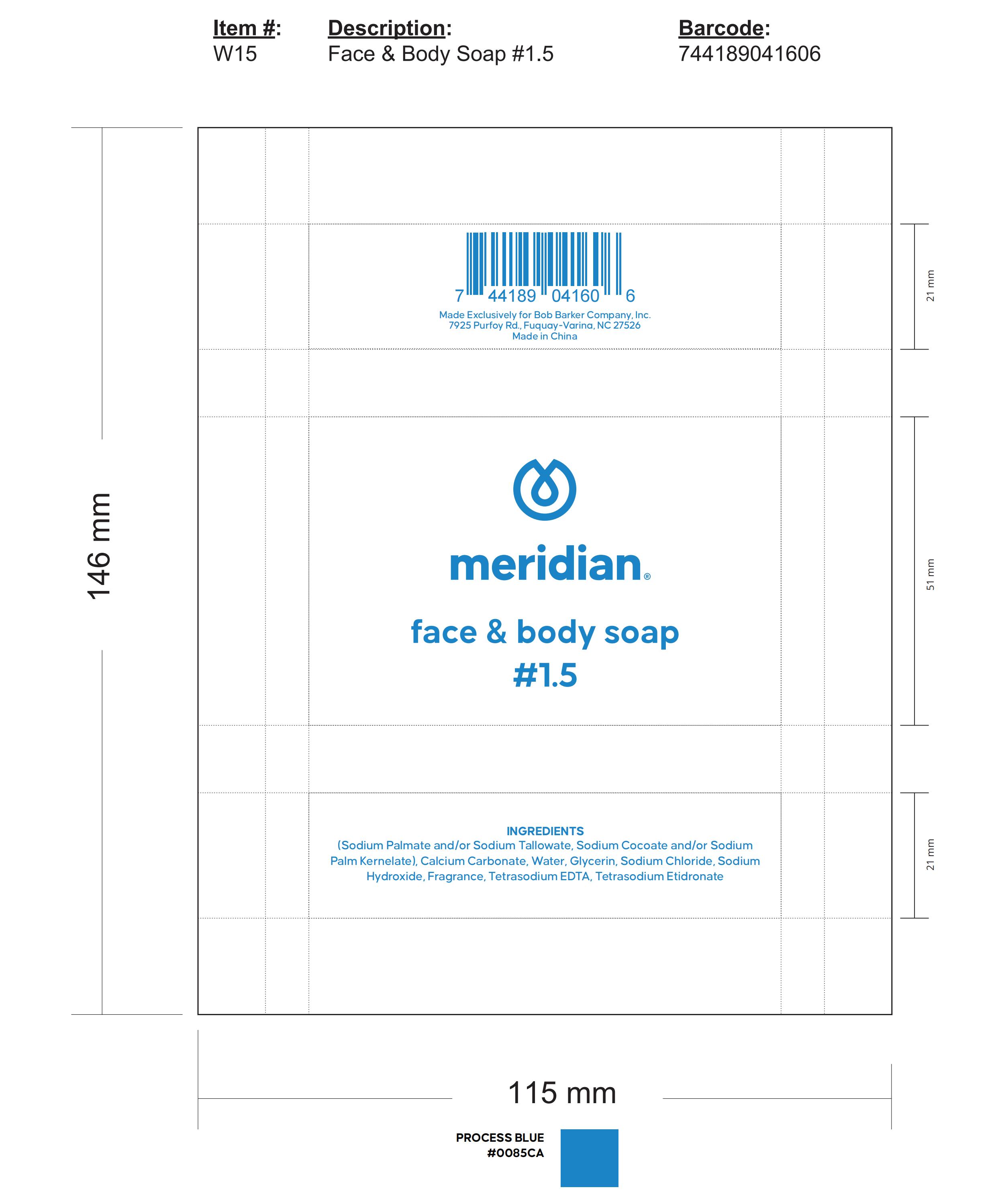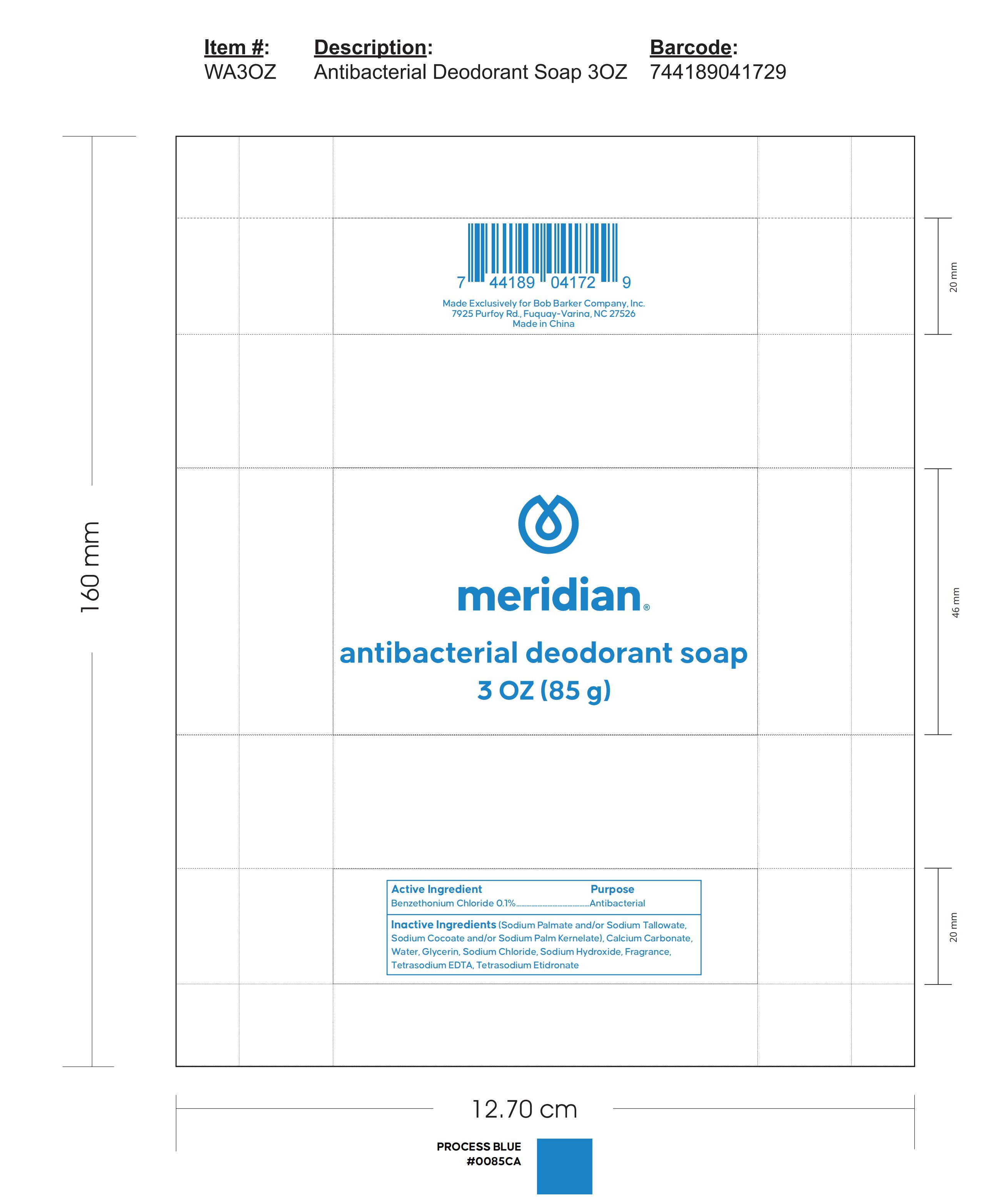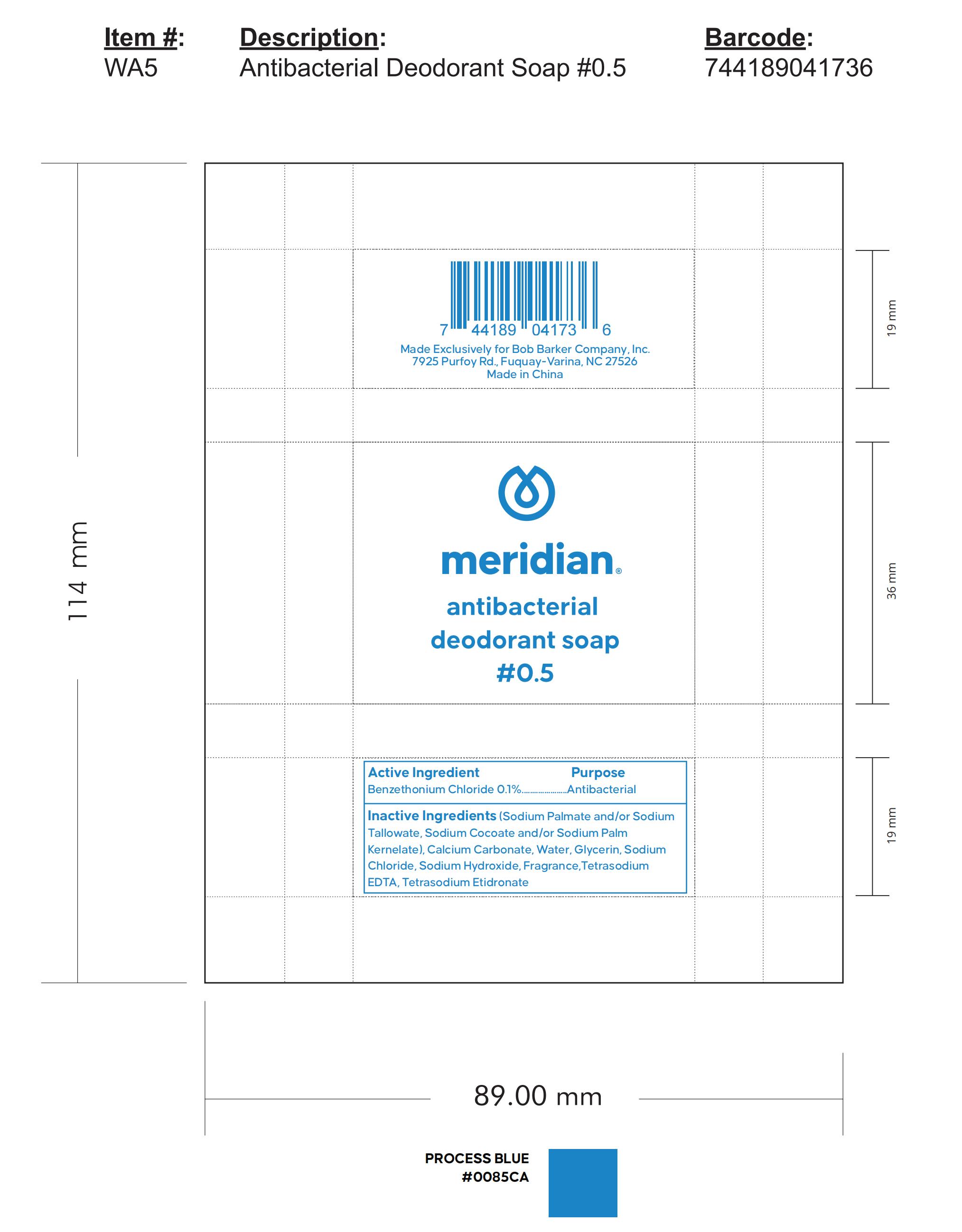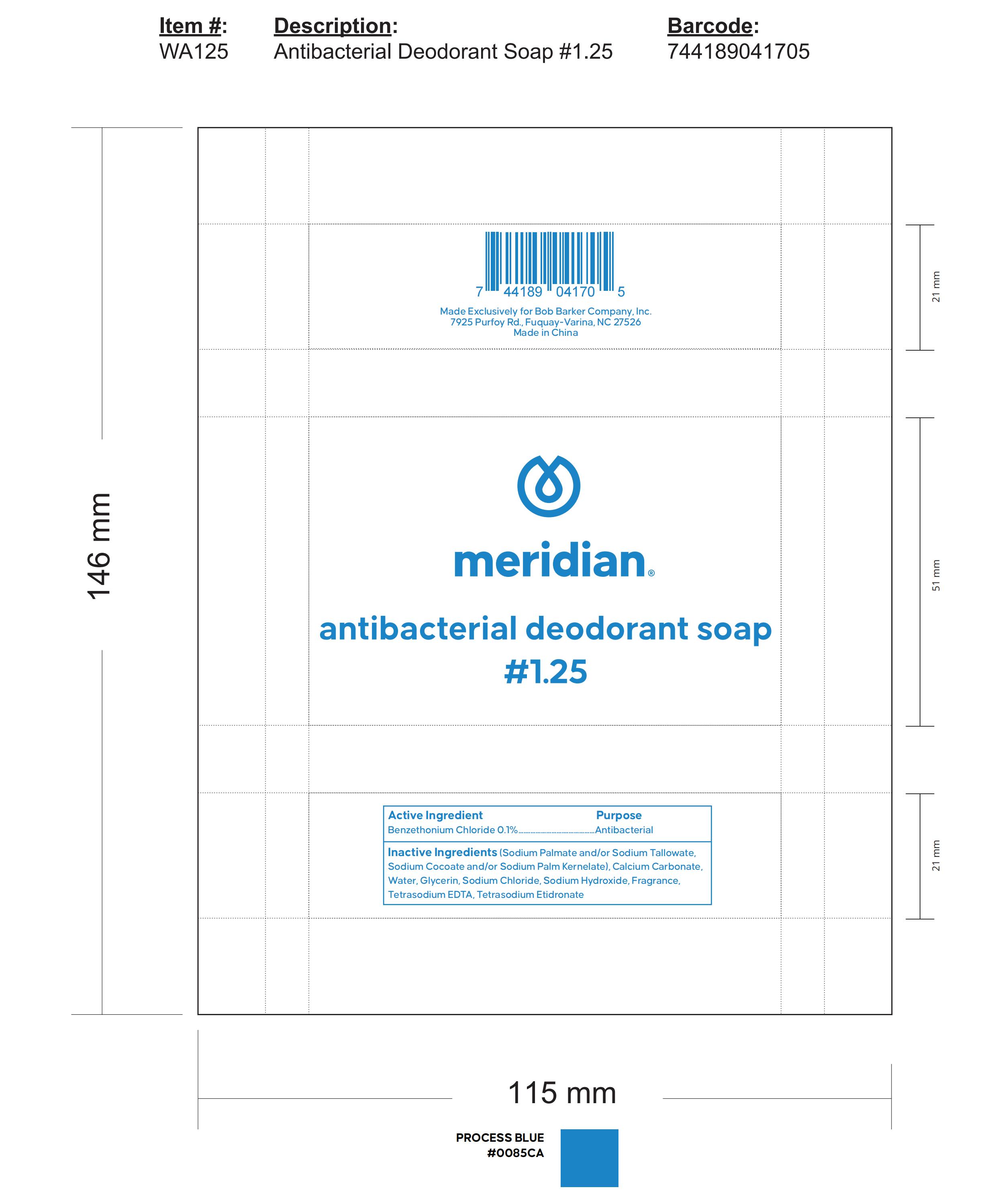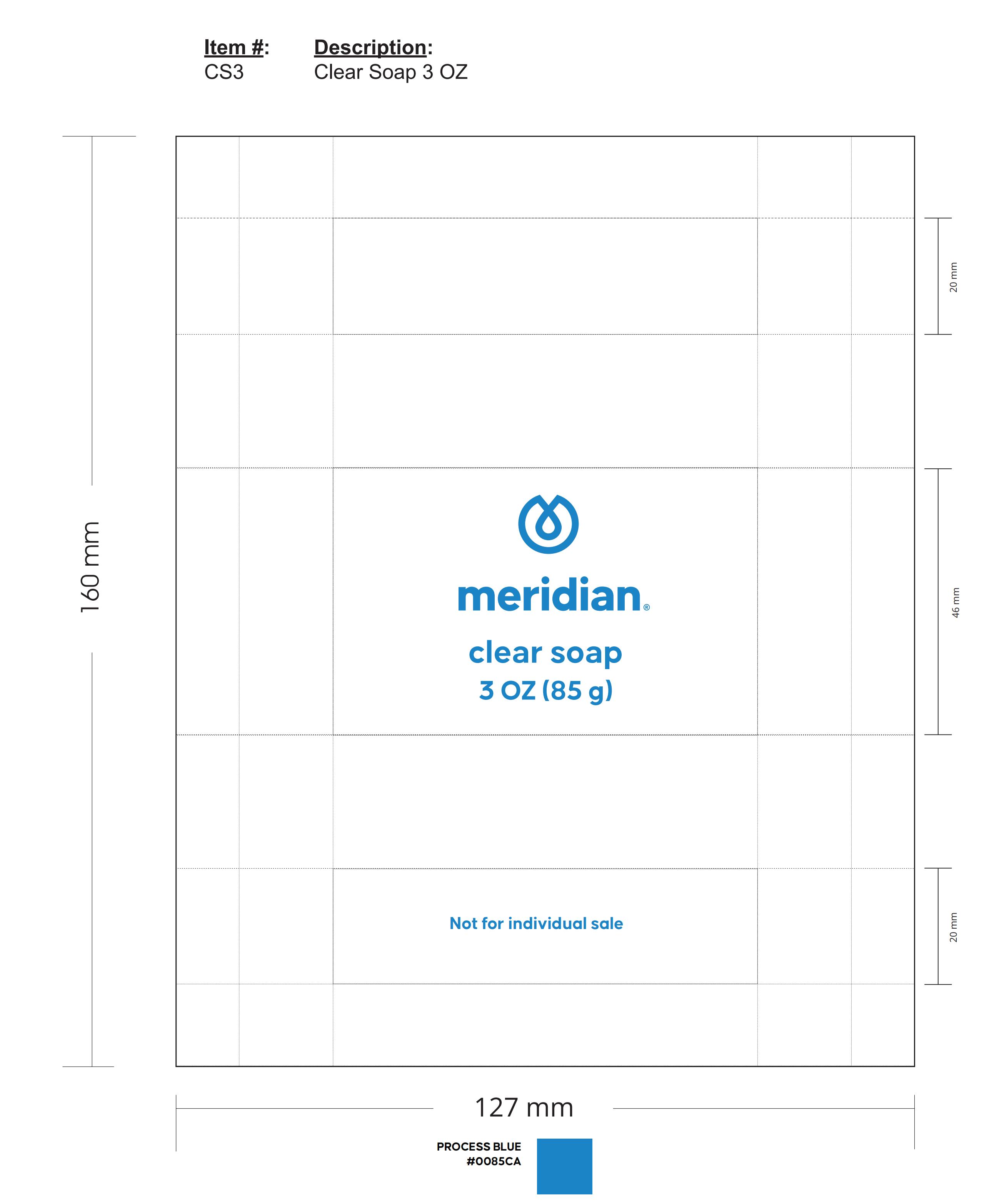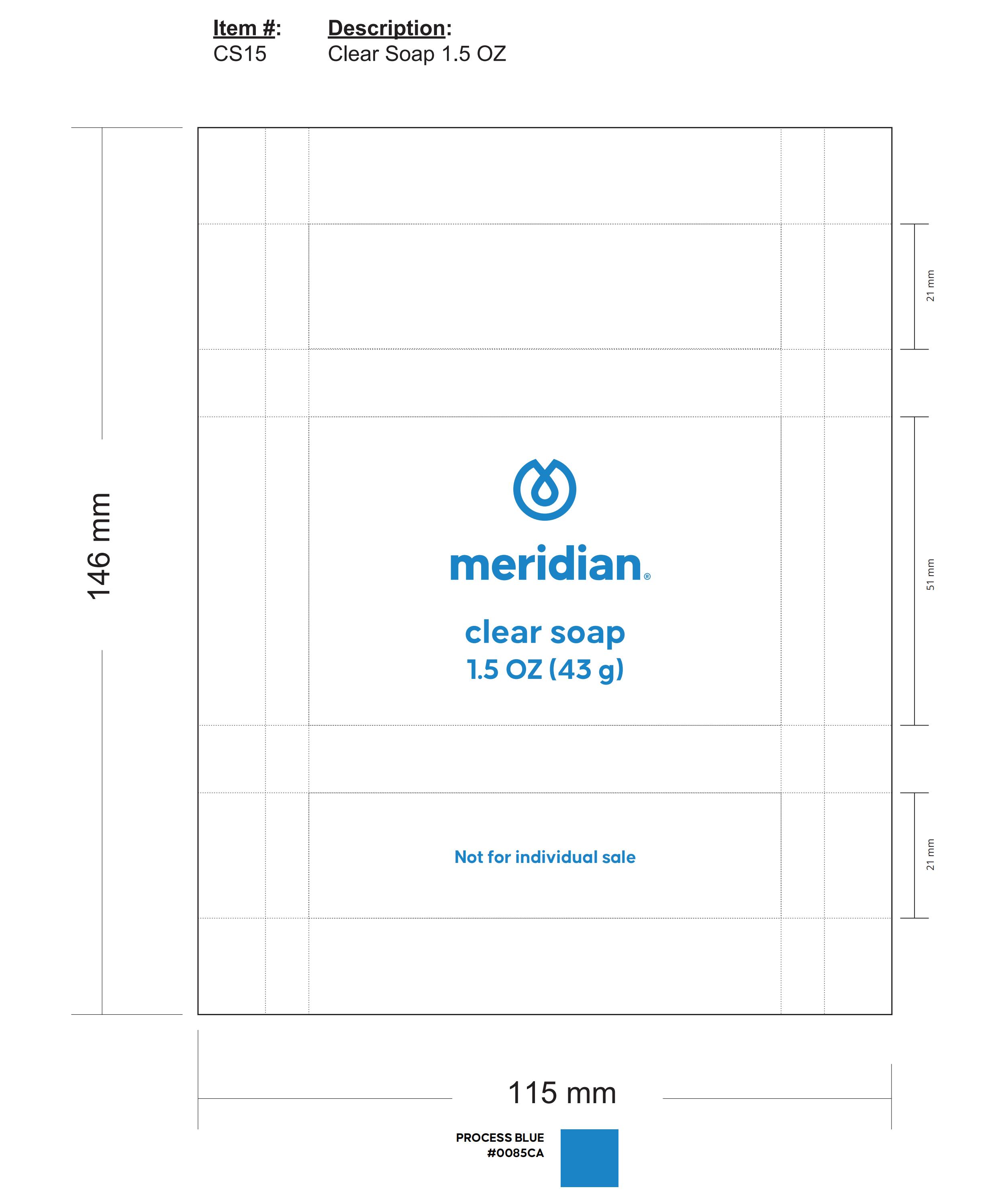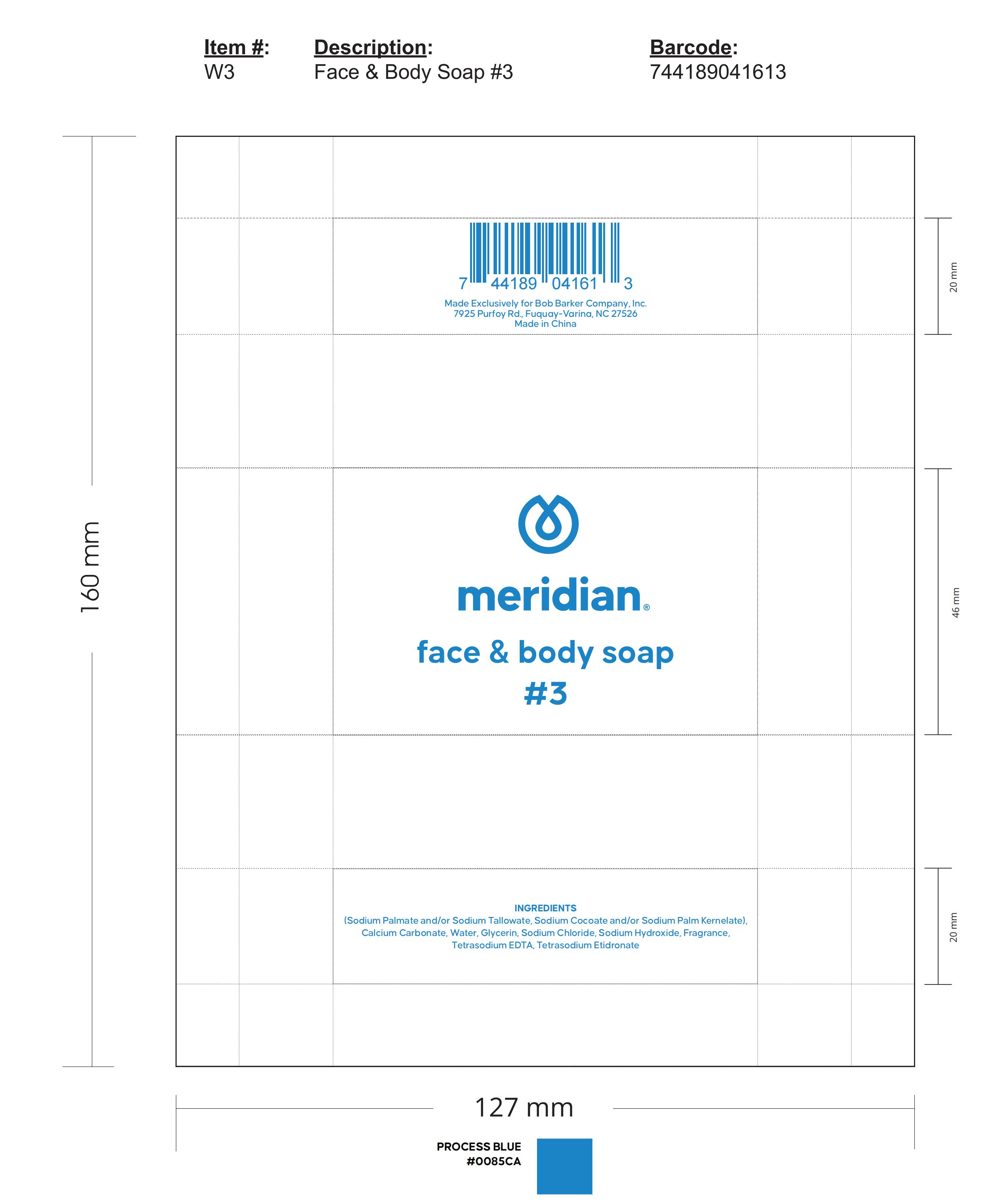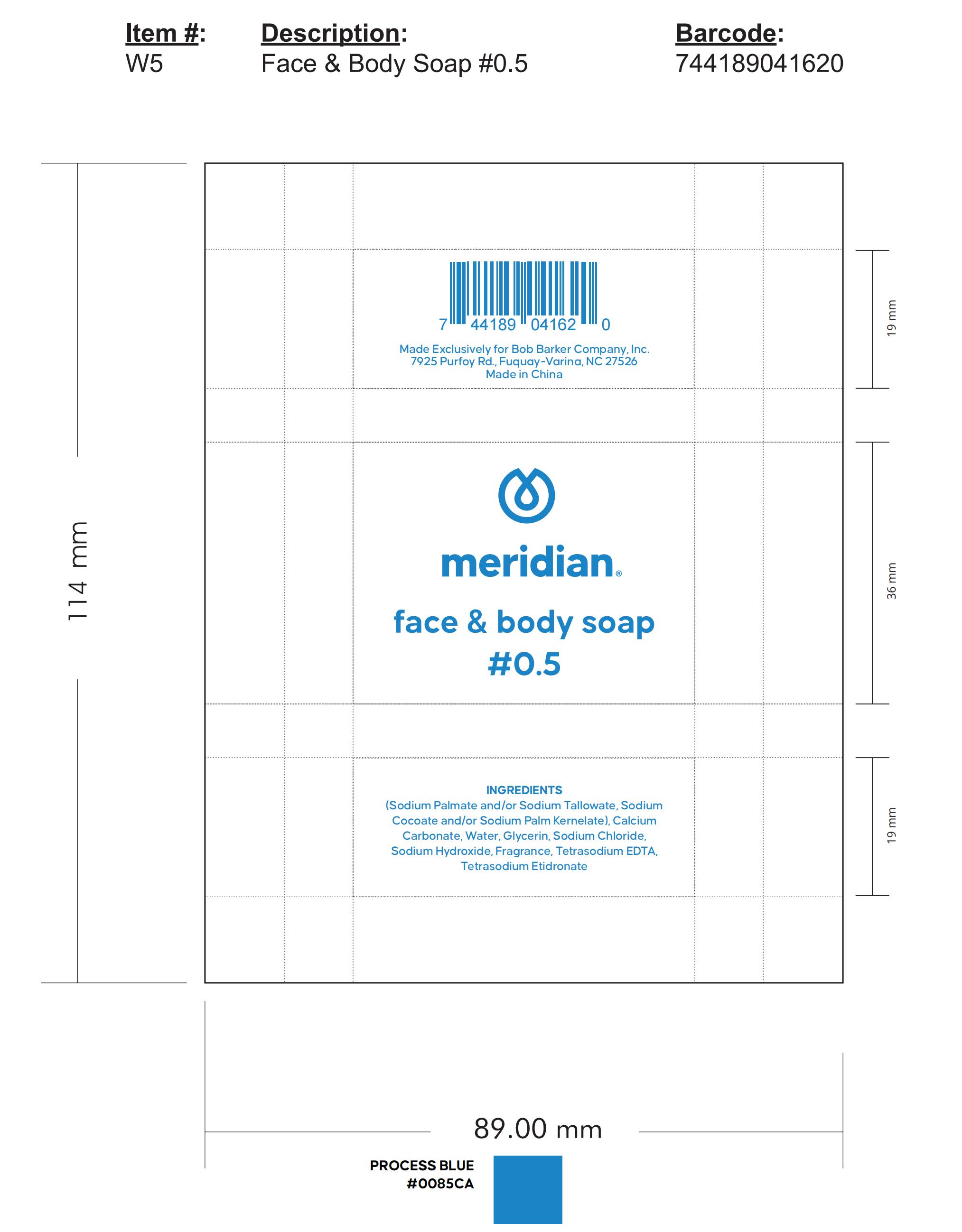 DRUG LABEL: meridian clear
NDC: 51543-0002 | Form: SOAP
Manufacturer: Yangzhou Safepure Daily Chemical Cleaning Products Co.,ltd.
Category: otc | Type: HUMAN OTC DRUG LABEL
Date: 20251126

ACTIVE INGREDIENTS: SODIUM PALM KERNELATE 20 g/100 g; SODIUM PALMATE 21.5 g/100 g; SODIUM COCOATE 7.05 g/100 g
INACTIVE INGREDIENTS: SODIUM CHLORIDE 0.25 g/100 g; BENZETHONIUM CHLORIDE 0.2 g/100 g; FRAGRANCE 13576 2 g/100 g; SODIUM HYDROXIDE 6.7 g/100 g; CALCIUM CARBONATE 30 g/100 g; WATER 10 g/100 g; GLYCERIN 1.5 g/100 g; TETRASODIUM EDTA 0.6 g/100 g; ETIDRONATE TETRASODIUM 0.2 g/100 g

INACTIVE INGREDIENT

Calcium Carbonate

Water

Glycerin

Sodium Chloride

Sodium Hydroxide

Fragrance

Etidronate Tetrasodium

Tetrasodium EDTA

Benzethonium Chloride

ACTIVE INGREDIENT

Product 1：

Sodium Palmate 21.6%

Sodium Palm Kernelate 20%

Sodium Cocoate 7.05%

Product 2：

Sodium Palmate 21.5%

Sodium Palm Kernelate 20%

Sodium Cocoate 7.05%

DOSAGE AND ADMINISTRATION

INSIRUCTIONS:Wet hands tharoughly with produet and allow to dry without wiping

WARNINGS

For ecternal use only.

KEEP OUT OF REACH OF CHILDREN

Keep out of eyes: In case of contact with eyes,please fush thoroughly with water.

PURPOSE

Sterilization

INDICATIONS AND USAGE

USES:To decrease boeteriaon the skin that could causedisease.